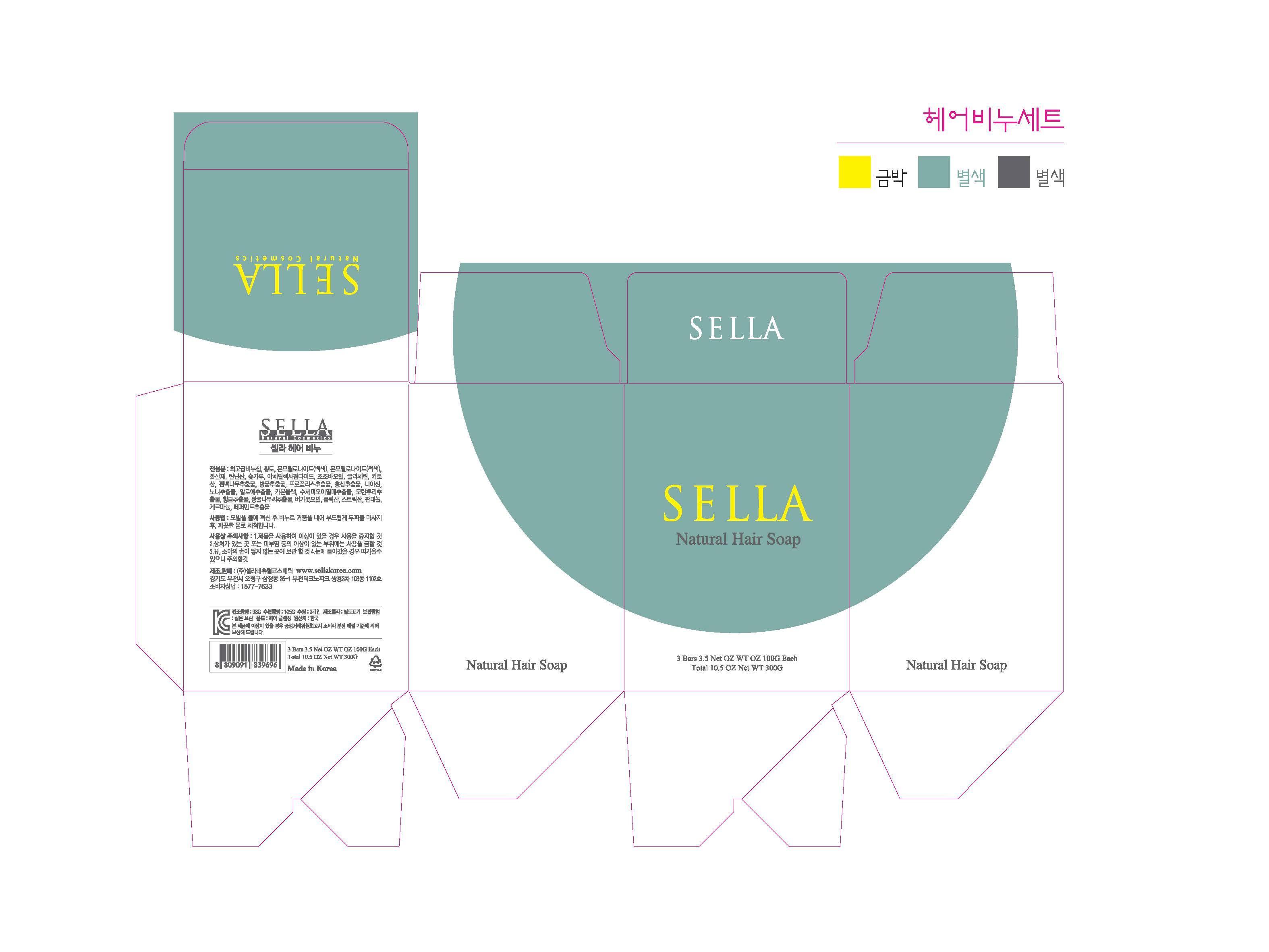 DRUG LABEL: SELLA NATURAL HAIR
NDC: 69603-1201 | Form: SOAP
Manufacturer: Sella Natural Cosmetics Co.,Ltd.
Category: otc | Type: HUMAN OTC DRUG LABEL
Date: 20150211

ACTIVE INGREDIENTS: GLYCERIN 0.4 g/100 g
INACTIVE INGREDIENTS: NIACINAMIDE; JOJOBA OIL

Drug Facts

ACTIVE INGREDIENT

glycerine

INACTIVE INGREDIENT

soap base, yellow ocher, tannic acid, chitosan, niacinamide, folic acid, panthenol etc

PURPOSE

skin protectant

keep out of reach of the children

INDICATIONS AND USAGE

wash softly after 2 minutes massage with soapsuds (repeat)

WARNINGS

・Stop using the product when you have skin problems or the product disagrees with your skin
・Stop using the product immediately and consult a dermatologist if you have redness, swelling, itching or irritation on the skin while or after using the product.
・Don't place the product in any place where it will be subjected to extremely high or low temperatures or direct sunlight.

DOSAGE AND ADMINISTRATION

for external use only